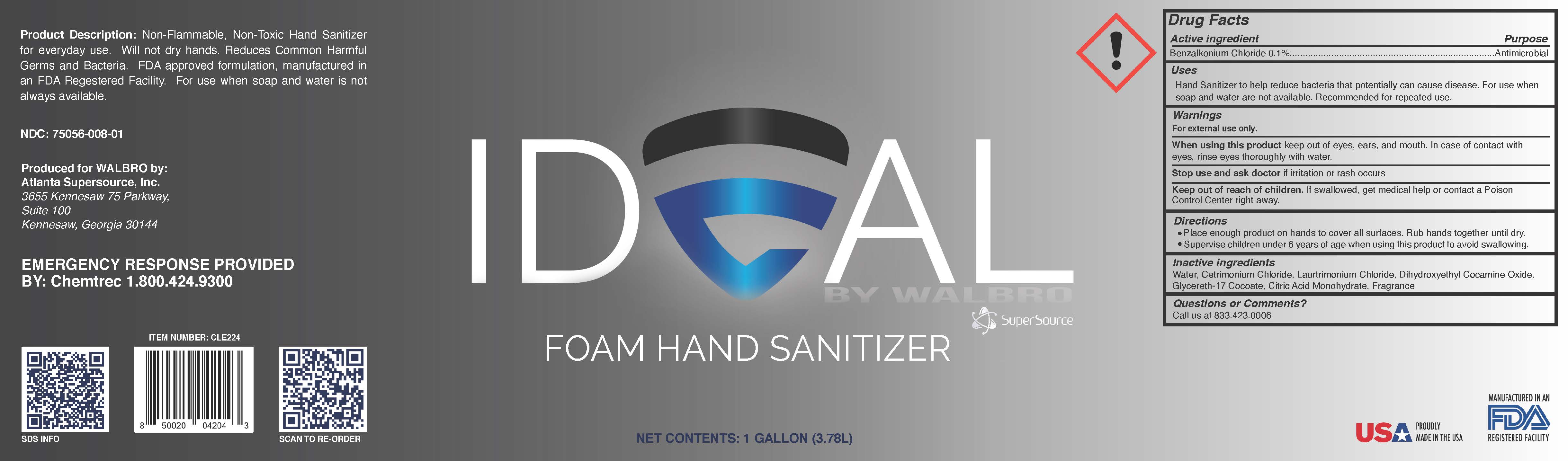 DRUG LABEL: Hand Sanitizer
NDC: 75056-008 | Form: AEROSOL, FOAM
Manufacturer: Atlanta Supersource, Inc.,
Category: otc | Type: HUMAN OTC DRUG LABEL
Date: 20221205

ACTIVE INGREDIENTS: BENZALKONIUM CHLORIDE 0.1 g/100 g
INACTIVE INGREDIENTS: WATER 99.8703 g/100 g; LAURTRIMONIUM CHLORIDE 0.0099 g/100 g; CETRIMONIUM CHLORIDE 0.0099 g/100 g; DIHYDROXYETHYL COCAMINE OXIDE 0.0099 g/100 g

Ideal Foam Hand Sanitizer

Ideal Foam Hand Sanitizer

Product Description: Non-Flammable, Non-Toxic Hand Sanitizer for everyday use. Will not dry hands. Reduces Common Harmful Germs and Bacteria. FDA approved formulation, manufactured in an FDA Registered Facility. For use when soap and water is not always available.

NDC: 75056-0008-01

Produced for WALBRO by:

Atlanta Supersource, Inc.

3655 Kennesaw 75 Parkway:

Suite 100

Kennesaw, Georgia 30144

EMERGENCY RESPONSE PROVIDED BY: Chemtrec 1.800.424.9300

Item Number: CLE224

Active Ingredient (s)

Benzalkonium Chloride 0.1%

Purpose

Antimicrobial

Uses

Hand Sanitizer to help reduce bacteria that can potentially cause disease. For use when soap and water are not available. Recommended for repeated use.

Warnings

For external use only.

When using this product

keep our to eyes, ears, and mouth. In case of contact with eyes, rinse eyes thoroughly with water.

Stop use and ask doctor

If irritation or rash occurs.

Keep out of reach of children. If swallowed, get medical help or contact a Poison Control Center right away.

Directions

Place enough product on hands to cover all surfaces. Rub hands together until dry. Supervise children under 6 years of age when using this product to avoid swallowing.

Inactive Ingredients

Water, Cetrimonium Chloride, Laurtrimonium Chloride, Dihydroxyethyl Cocamine Oxide

Glycereth-17, Citric Acid Monohydrate - these are not on the Product Data Sheet and Katie explained they do not nee to be listed.

Questions or Comments?

Call us at 833.423.0006